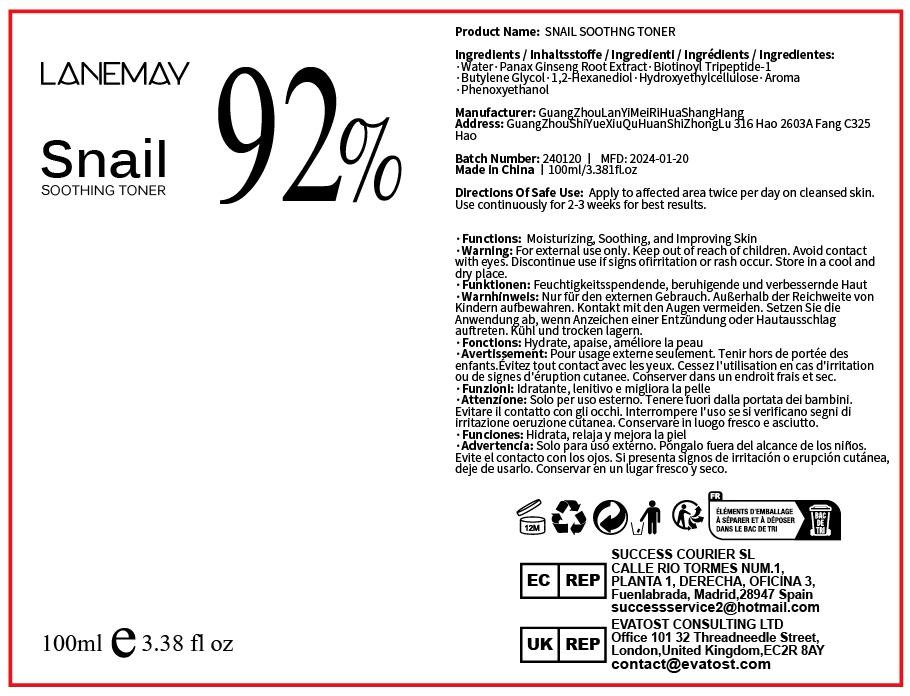 DRUG LABEL: SNAIL SOOTHING TONER
NDC: 84025-028 | Form: LIQUID
Manufacturer: Guangzhou Yanxi Biotechnology Co., Ltd
Category: otc | Type: HUMAN OTC DRUG LABEL
Date: 20240402

ACTIVE INGREDIENTS: PANAX GINSENG ROOT WATER 10 mg/60 mL; BIOTINOYL TRIPEPTIDE-1 8 mg/60 mL
INACTIVE INGREDIENTS: WATER

DOSAGE AND ADMINISTRATION

use as a normal toner

WARNINGS

For external use only.

INACTIVE INGREDIENT

Aqua

INDICATIONS AND USAGE

For daily facial care

Keep out of reach of children.

PURPOSE

Moisturizing, Soothing, and Improving Skin